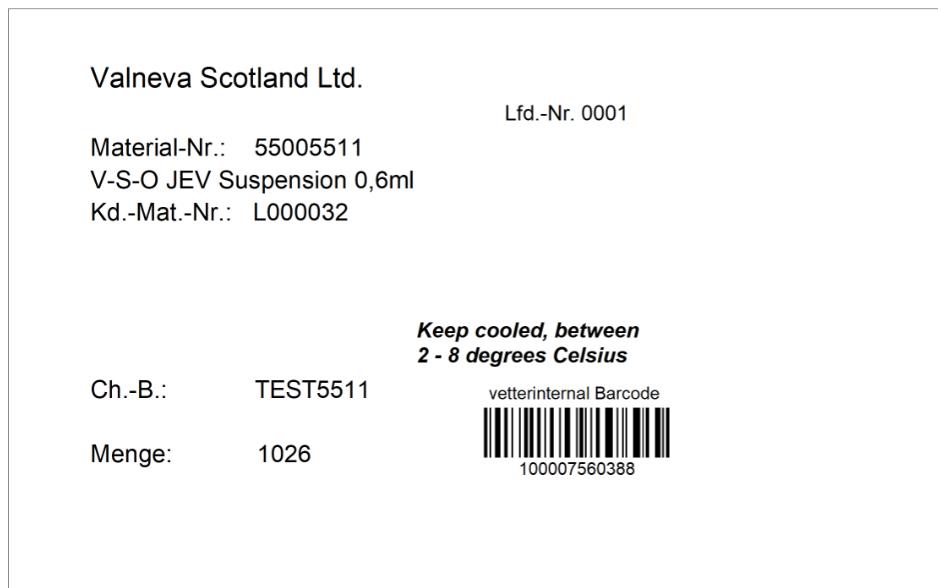 DRUG LABEL: Ixiaro
NDC: 62195-051 | Form: INJECTION, SUSPENSION
Manufacturer: Vetter Pharma Fertigung GmbH & Co. KG
Category: other | Type: VACCINE LABEL
Date: 20251125

ACTIVE INGREDIENTS: JAPANESE ENCEPHALITIS VIRUS STRAIN SA 14-14-2 ANTIGEN (FORMALDEHYDE INACTIVATED) 6 ug/0.5 mL

Ixiaro